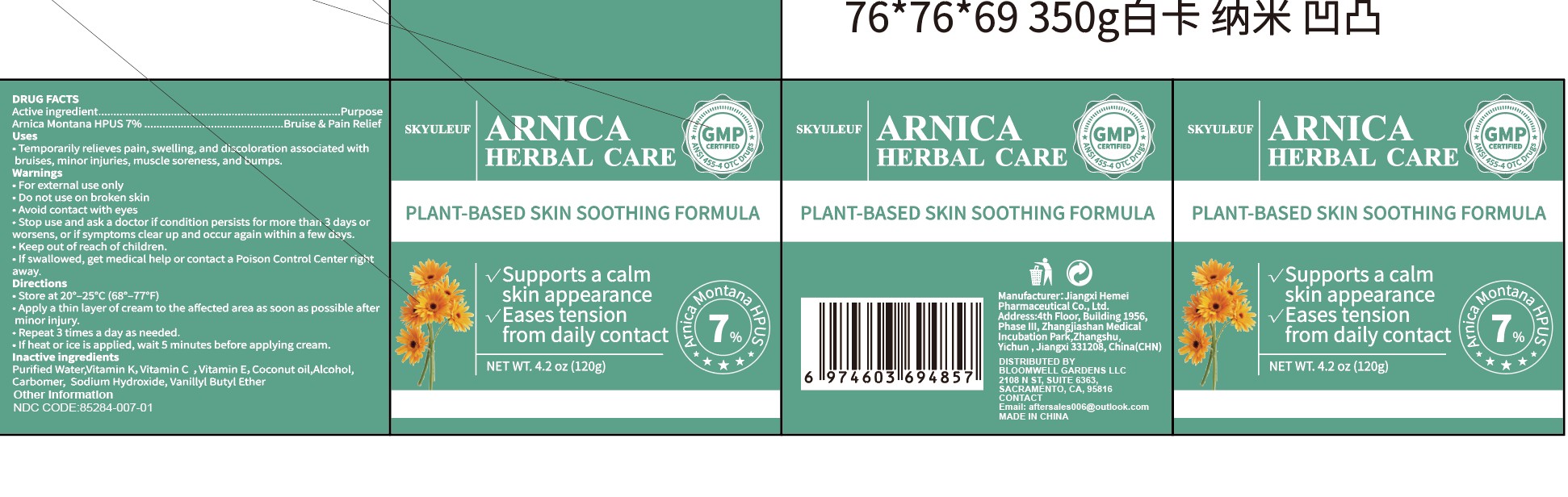 DRUG LABEL: ARNICA HERBAL CARE cream
NDC: 85284-007 | Form: CREAM
Manufacturer: BLOOMWELL GARDENS LLC
Category: otc | Type: HUMAN OTC DRUG LABEL
Date: 20250801

ACTIVE INGREDIENTS: ARNICA MONTANA 7 g/100 g
INACTIVE INGREDIENTS: VITAMIN E POLYETHYLENE GLYCOL SUCCINATE; VITAMIN K-DEPENDENT PROTEIN C; ALCOHOL; SODIUM HYDROXIDE; VANILLYL BUTYL ETHER; WATER; CARBOMER; COCONUT OIL

Active ingredient, ...........................Arnica Montana HPUs 7%

Inactive ingredients

Purified Water, Vitamin K, Vitamin C , Vitamin E, Coconut oil, Alcohol

Carbomer, sodium Hydroxide, Vanillyl Butyl Ether

Purpose, .......................... Bruise & Pain Relief

Directions

.Apply a thin layer of cream to the affected area as soon as possible after minor injury.

.Repeat 3 times a day as needed.

.If heat or ice is applied, wait 5 minutes before applying cream.

Warnings

For external use only

. Do not use on broken skin

. Avoid contact with eyes

*Stop use and ask a doctor if condition persists for more than 3 days or worsens, or if symptoms clear up and occur again within a few days.

*Keep out of reach of children.

If swallowed, get medical help or contact a Poison Control Center right away.

Uses

Temporarily relieves pain, swelling, and discoloration associated with

bruises, minor injuries, muscle soreness, and bumps.